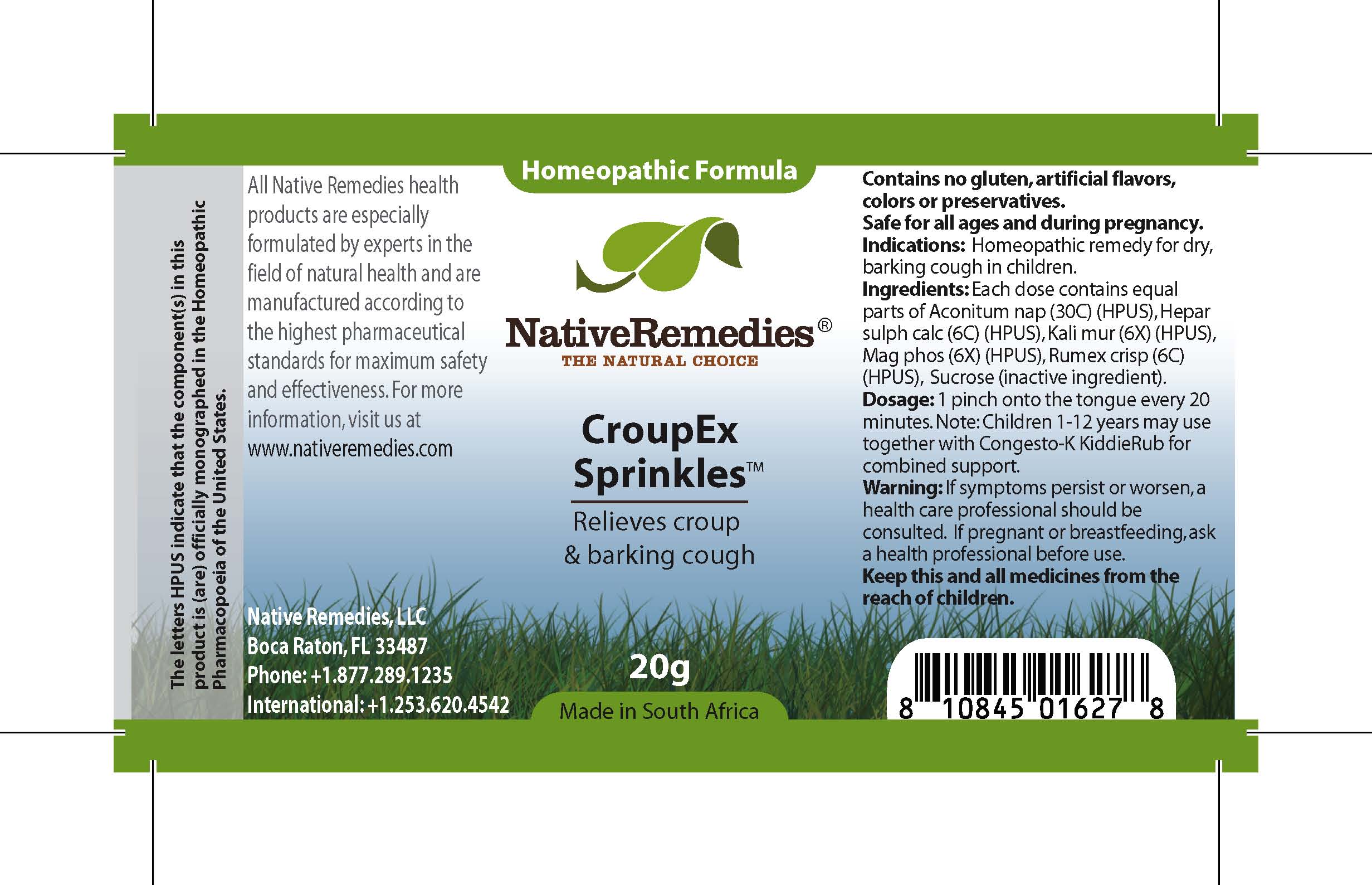 DRUG LABEL: CroupEx Sprinkles
NDC: 68647-106 | Form: GRANULE
Manufacturer: Feelgood Health
Category: homeopathic | Type: HUMAN OTC DRUG LABEL
Date: 20100722

ACTIVE INGREDIENTS: ACONITUM NAPELLUS 30 [hp_C]/40 mg; CALCIUM SULFIDE 6 [hp_C]/40 mg; POTASSIUM CHLORIDE 6 [hp_X]/40 mg; MAGNESIUM PHOSPHATE 6 [hp_X]/40 mg; RUMEX CRISPUS POLLEN 6 [hp_C]/40 mg
INACTIVE INGREDIENTS: SUCROSE 20000 mg/20000 mg

CROUPEX SPRINKLES

PURPOSE

Relieves croup and barking cough

INDICATIONS AND USAGE

Indications: Homeopathic remedy for dry, barking cough in children.

DOSAGE AND ADMINISTRATION

Dosage: 1 pinch onto the tongue every 20 minutes. Children 1-12 years may use together with Congesto-K KiddieRub™ for combined support.

GENERAL PRECAUTIONS

Caution: If symptoms persist or worsen, a health care professional should be consulted.Keep this and all medicines from the reach of children.

ACTIVE INGREDIENT

Ingredients: Each dose contains equal parts of Aconitum nap (30C) (HPUS), Hepar sulph calc (6C) (HPUS), Kali mur (6X) (HPUS), Mag phos (6X) (HPUS), Rumex crisp (6C) (HPUS)

Sucrose (inactive ingredient).

PREGNANCY

If pregnant or breastfeeding, ask a health professional before use.

WARNINGS

Contains no gluten, artificial flavors, colors or preservatives.Safe for all ages and during pregnancy.

PATIENT COUNSELING INFORMATION

All Native Remedies health products are especially formulated by experts in the field of natural health and are manufactured according to the highest pharmaceutical standards for maximum safety and effectiveness. For more information, visit us at www.nativeremedies.com

Distributed by

Native Remedies, LLC

6531 Park of Commerce Blvd.

Suite 160

Boca Raton, FL 33487

Phone: 1.877.289.1235

International: + 1.561.999.8857

The letters HPUS indicate that the component(s) in this product is (are) officially monographed in the Homeopathic Pharmacopoeia of the United States.

KEEP OUT OF REACH OF CHILDREN

Keep this and all medicines from the reach of children.